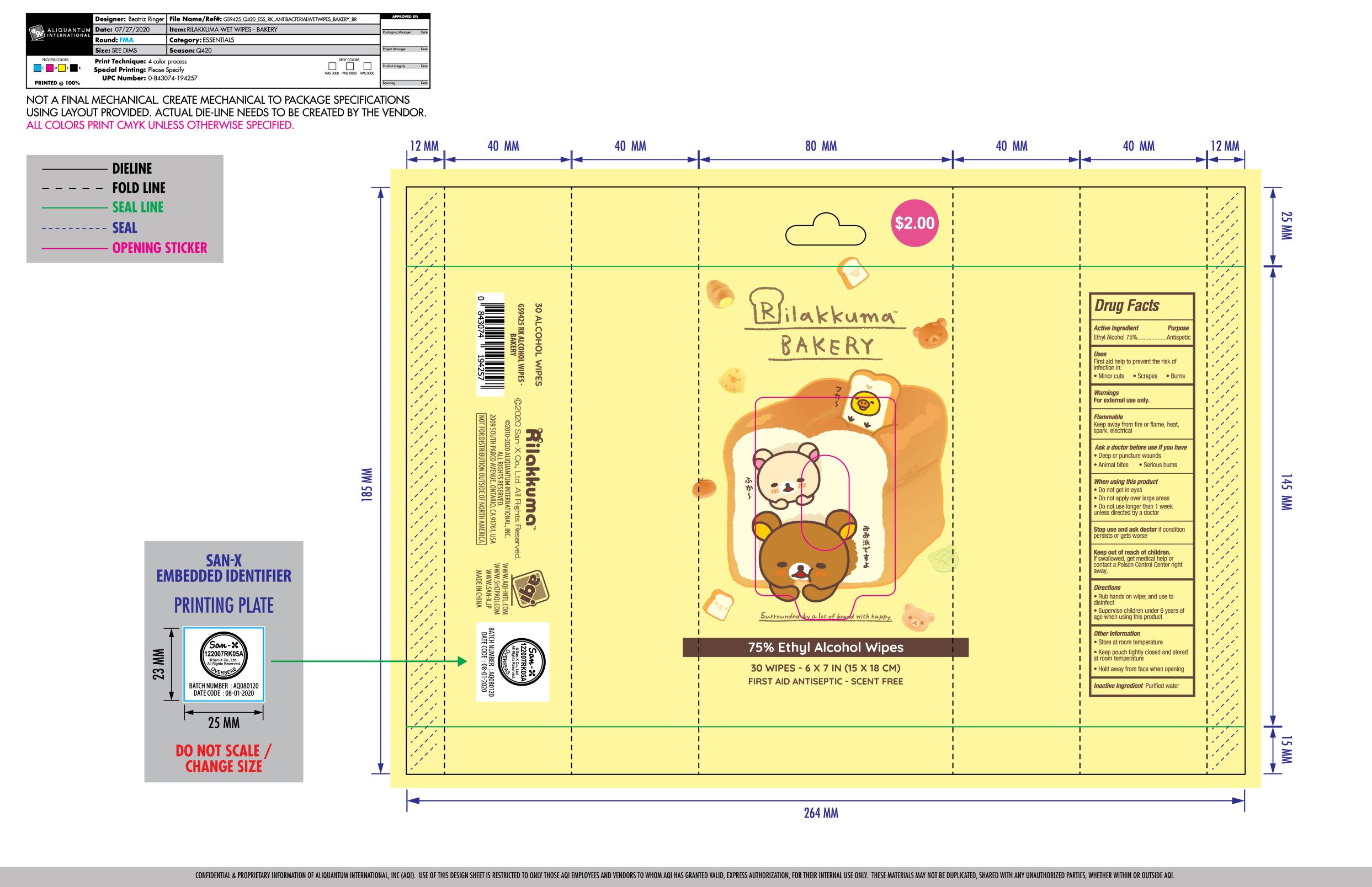 DRUG LABEL: Disinfecting Wipes
NDC: 40562-016 | Form: CLOTH
Manufacturer: Anhui Hanbon Daily Chemical Co., Ltd.
Category: otc | Type: HUMAN OTC DRUG LABEL
Date: 20220123

ACTIVE INGREDIENTS: ALCOHOL 75 mL/100 mL
INACTIVE INGREDIENTS: WATER

Hanbon
Disinfecting Wipes
30PCS 40562-016-01

Active Ingredient(s)

Ethyl Alcohol 75%

Purpose

Antispetic

Use

First aid help to prevent the risk of infection in:

- Minor cuts
- Scrapes
- Burns

Warnings

- For external use only
- Flammable. Keep away from fire or flame, heat, spark, electrical

Ask a doctor before use if you have

- Deep or puncture wounds
- Animal bites
- Serious burns

When using this product

- Do not get in eyes
- Do not apply over large areas
- Do not use longer than 1 week
- unless directed by a doctor

Stop use and ask doctor if condition persists or gets worse.

KEEP OUT OF REACH OF CHILDREN

If swallowed, get medical help or contact a Posion Control Center right away.

OTHER SAFETY INFORMATION

- Store at room temperature
- Keep pouch tightly closed and stored at room temperature
- Hold away from face when opening

Directions

- Rub hands on wipe; and use to disinfect
- Supervise children under 6 years of age when using this product

Inactive ingredients

Purified water.

Package Label - Principal Display Panel

30 PATCH in 1 PACKET NDC: 40562-016-01